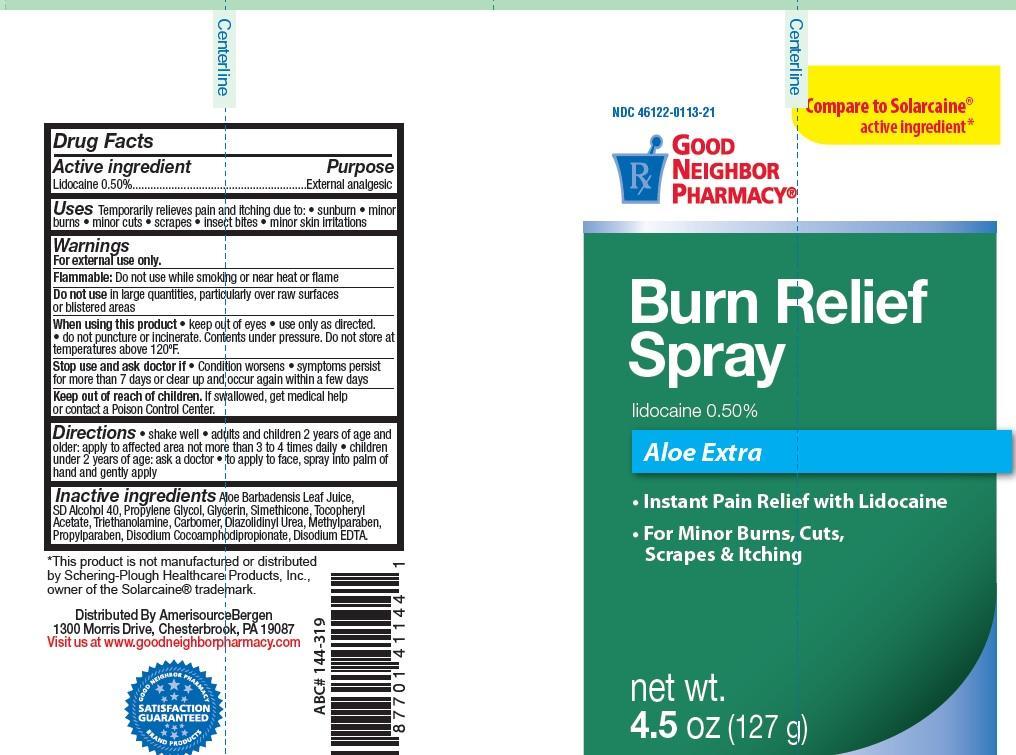 DRUG LABEL: Good Neighbor Pharmacy Burn Relief
NDC: 46122-113 | Form: SPRAY
Manufacturer: AmerisourceBergen Drug Corporation
Category: otc | Type: HUMAN OTC DRUG LABEL
Date: 20150717

ACTIVE INGREDIENTS: LIDOCAINE .50 g/100 g
INACTIVE INGREDIENTS: ALOE VERA LEAF; ALCOHOL; PROPYLENE GLYCOL; GLYCERIN; SIMETONE; .ALPHA.-TOCOPHEROL ACETATE; TROLAMINE; CARBOMER HOMOPOLYMER TYPE C; DIAZOLIDINYL UREA; METHYLPARABEN; PROPYLPARABEN; DISODIUM COCOAMPHODIPROPIONATE; EDETATE DISODIUM

Good Neighbor Pharmacy Burn Relief

Active ingredient

Lidocaine 0.50%

Purpose

External analgesic

Uses

Temporarily relieves pain and itching due to: • sunburn • minor

burns • minor cuts • scrapes • insect bites • minor skin irritations

Warnings

For external use only.

Flammable: Do not use while smoking or near heat or flame

Do not use

in large quantities, particularly over raw surfaces or blistered areas

When using this product

• keep out of eyes • use only as directed.

• do not puncture or incinerate. Contents under pressure. Do not store at

temperatures above 120ºF.

Stop use and ask doctor if

Condition worsens • symptoms persist

for more than 7 days or clear up and occur again within a few days

Keep out of reach of children.

If swallowed, get medical help or contact a Poison Control Center.

Directions

• shake well • adults and children 2 years of age and

older: apply to affected area not more than 3 to 4 times daily • children

under 2 years of age: ask a doctor • to apply to face, spray into palm of

hand and gently apply

Inactive ingredients

Aloe Barbadensis Leaf Juice,

SD Alcohol 40, Propylene Glycol, Glycerin, Simethicone, Tocopheryl

Acetate, Triethanolamine, Carbomer, Diazolidinyl Urea, Methylparaben,

Propylparaben, Disodium Cocoamphodipropionate, Disodium EDTA.